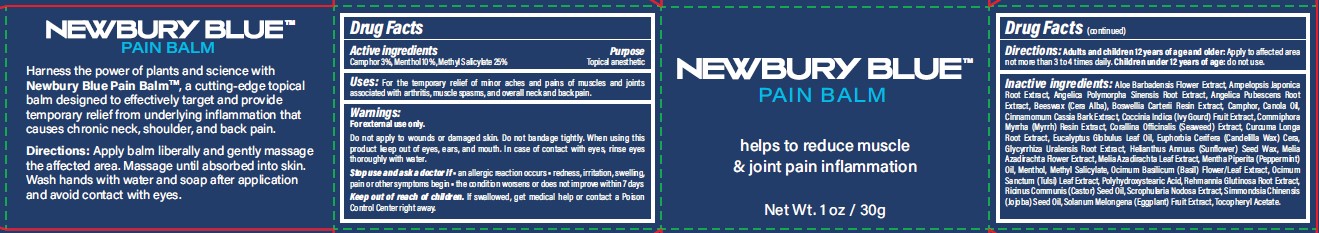 DRUG LABEL: NEWBURY BLUE PAIN BALM
NDC: 83501-101 | Form: OINTMENT
Manufacturer: Newbury Extracts, LLC
Category: otc | Type: HUMAN OTC DRUG LABEL
Date: 20240930

ACTIVE INGREDIENTS: METHYL SALICYLATE 25 g/100 mL; CAMPHOR (SYNTHETIC) 3 g/100 mL; MENTHOL 10 g/100 mL
INACTIVE INGREDIENTS: YELLOW WAX; CINNAMOMUM CASSIA WHOLE; CANOLA OIL; CORALLINA OFFICINALIS; AZADIRACHTA INDICA LEAF; SOLANUM MELONGENA WHOLE; OCIMUM BASILICUM WHOLE; HOLY BASIL LEAF; FRANKINCENSE; COCCINIA GRANDIS WHOLE; CANDELILLA WAX; HELIANTHUS ANNUUS SEED WAX; SCROPHULARIA NODOSA; ALOE VERA LEAF; ANGELICA PUBESCENS ROOT; AMPELOPSIS JAPONICA ROOT; ANGELICA POLYMORPHA ROOT; CURCUMA LONGA WHOLE; EUCALYPTUS GLOBULUS LEAF; AZADIRACHTA INDICA FLOWER; PEPPERMINT OIL; POLYHYDROXYSTEARIC ACID (2300 MW); JOJOBA OIL; GLYCYRRHIZA URALENSIS ROOT; CASTOR OIL; REHMANNIA GLUTINOSA ROOT; .ALPHA.-TOCOPHEROL ACETATE

Westside Pain Specialists (as PLD) - Pain Cream (83501-101)

ACTIVE INGREDIENTS

Camphor 3%

Menthol 10%

Methyl Salicylate 25%

PURPOSE

TOPICAL ANESTHETIC

USES

FOR RELIEF FROM ACHES, ARTHRITIS, MUSCLE SPASMS, AND OVERALL NECK AND BACK PAIN.

WARNINGS

FOR EXTERNAL USE ONLY. WHEN USING THIS PRODUCT KEEP OUT OF EYES, EARS, AND MOUTH. IN CASE OF CONTACT WITH EYES, RINSE EYES THOROUGHLY WITH WATER.

KEEP OUT OF REACH OF CHILDREN. IF SWALLOWED, GET MEDICAL HELP OR CONTACT A POISON CONTROL CENTER RIGHT AWAY.

STOP USE AND ASK A DOCTOR IF:

- AN ALLERGIC REACTION OCCURS
- REDNESS, IRRITATION, SWELLING, PAIN OR OTHER SYMPTOMS BEGIN.
- THE CONDITION WORSENS OR DOES NOT IMPROVE WITHIN 7 DAYS

OTHER INFORMATION

STORE BETWEEN 15-30°C (59-86°F). AVOID FREEZING AND EXCESSIVE HEAT ABOVE 40°C (104°F).

DIRECTIONS

APPLY BALM LIBERALLY AND GENTLY MASSAGE THE AFFECTED AREA. MASSAGE UNTIL ABSORBED INTO SKIN. WASH HANDS WITH WATER AND SOAP AFTER APPLICATION AND AVOID CONTACT WITH EYES. CHILDREN UNDER 18 YEARS OF AGE SHOULD CONSULT A PHYSICIAN BEFORE USE.

INACTIVE INGREDIENTS

ALOE BARBADENSIS FLOWER EXTRACT, AMPELOPSIS JAPONICA ROOT EXTRACT, ANGELICA POLYMORPHA SINENSIS ROOT EXTRACT, ANGELICA PUBESCENS ROOT EXTRACT, BEESWAX (CERA ALBA), BOSWELLIA CARTERII RESIN EXTRACT, CAMPHOR, CANOLA OIL, CINNAMOMUM CASSIA BARK EXTRACT, COCCINIA INDICA (IVY GOURD) FRUIT EXTRACT, CORALLINA OFFICINALIS (SEAWEED) EXTRACT, CURCUMA LONGA ROOT EXTRACT, EUCALYPTUS GLOBULUS LEAF OIL, EUPHORBIA CERIFERA (CANDELILLA WAX) CERA, GLYCYRRHIZA URALENSIS ROOT EXTRACT, HELIANTHUS ANNUUS (SUNFLOWER) SEED WAX, MELIA AZADIRACHTA FLOWER EXTRACT, MELIA AZADIRACHTA LEAF EXTRACT, MENTHA PIPERITA (PEPPERMINT) OIL, MENTHOL, METHYL SALICYLATE, OCIMUM BASILICUM (BASIL) FLOWER/LEAF EXTRACT, OCIMUM SANCTUM (TULSI) LEAF EXTRACT, OLYHYDROXYSTEARIC ACID, REHMANNIA GLUTINOSA ROOT EXTRACT, RICINUS COMMUNIS (CASTOR) SEED OIL, SCROPHULARIA NODOSA EXTRACT, SIMMONDSIA CHINENSIS (JOJOBA) SEED OIL, SOLANUM MELONGENA (EGGPLANT) FRUIT EXTRACT, TOCOPHERYL ACETATE